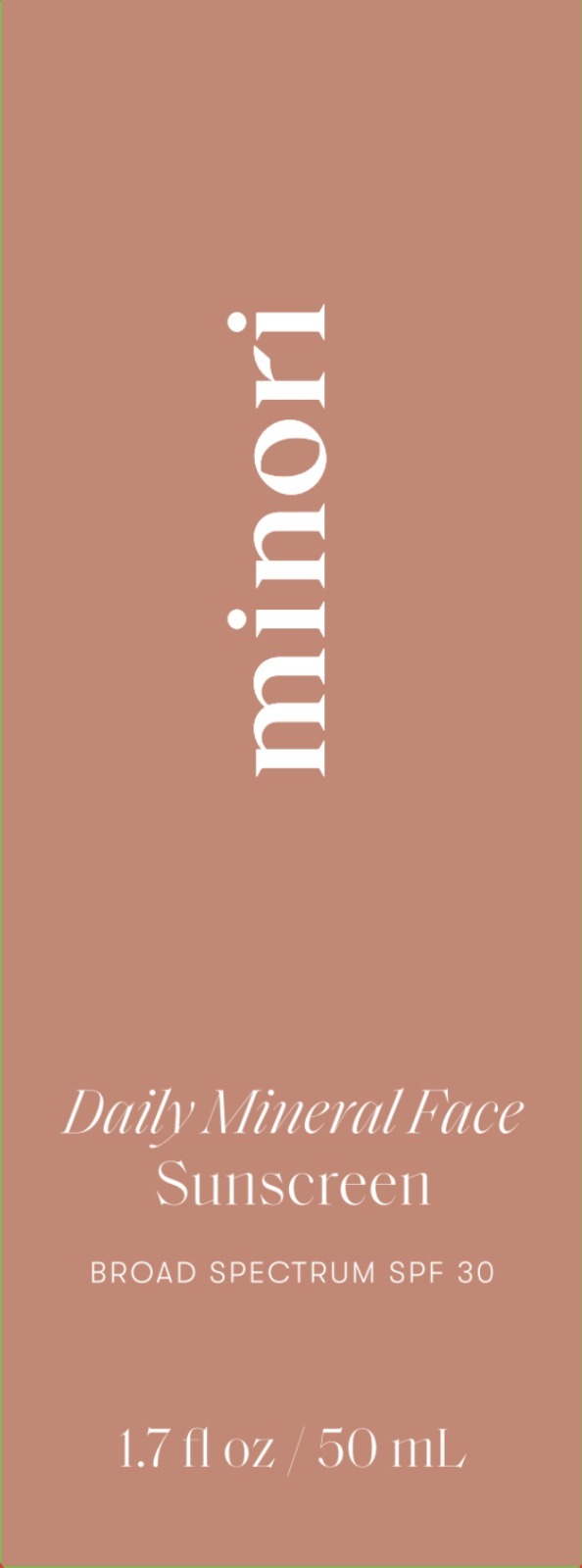 DRUG LABEL: Minori Daily  Mineral Face Sunscreen
NDC: 84321-101 | Form: LOTION
Manufacturer: Minori Inc.
Category: otc | Type: HUMAN OTC DRUG LABEL
Date: 20260112

ACTIVE INGREDIENTS: ZINC OXIDE 10 g/100 mL
INACTIVE INGREDIENTS: CETEARYL OLIVATE; GLYCERIN; BUTYLENE GLYCOL; TRIETHOXYCAPRYLYLSILANE; POMEGRANATE; ETHYLHEXYLGLYCERIN; FERRIC OXIDE YELLOW; FERROSOFERRIC OXIDE; FERRIC OXIDE RED; WATER; MEDIUM-CHAIN TRIGLYCERIDES; DIMETHICONE; CETOSTEARYL ALCOHOL; SORBITAN OLIVATE; CHAMOMILE; ALOE VERA LEAF; XANTHAN GUM; POLYGLYCERYL-3 DIISOSTEARATE; CETEARYL GLUCOSIDE; .ALPHA.-TOCOPHEROL ACETATE; PHENOXYETHANOL

Minori (as PLD): Daily Mineral Face Sunscreen (84321-101)

ACTIVE INGREDIENT

ZINC OXIDE 10%

PURPOSE

SUNSCREEN

USE

- HELPS PREVENT SUNBURN

WARNINGS

- FOR EXTERNAL USE ONLY.

- DO NOT USE ON DAMAGED OR BROKEN SKIN.

- WHEN USING THIS PRODUCT KEEP OUT OF EYES. RINSE WITH WATER TO REMOVE.

- STOP USE AND ASK A DOCTOR IF RASH OCCURS.

- KEEP OUT OF REACH OF CHILDREN. IF SWALLOWED, GET MEDICAL HELP OR CONTACT A POISON CONTROL CENTER RIGHT AWAY.

DIRECTIONS

- APPLY LIBERALLY 15 MINUTES BEFORE SUN EXPOSURE.
- CHILDREN UNDER 6 MONTHS OF AGE: ASK A DOCTOR.
- USE A WATER-RESISTANT SUNSCREEN IF SWIMMING OR SWEATING.
- REAPPLY AT LEAST EVERY 2 HOURS.
- SUN PROTECTION MEASURES: SPENDING TIME IN THE SUN INCREASES YOUR RISK OF SKIN CANCER AND EARLY SKIN AGING. TO DECREASE THIS RISK, REGULARLY USE A SUNSCREEN WITH A BROAD SPECTRUM SPF VALUE OF 15 OR HIGHER AND OTHER SUN PROTECTION MEASURES INCLUDING:
- LIMIT TIME IN THE SUN, ESPECIALLY FROM 10 A.M. - 2 P.M.
- WEAR LONG-SLEEVED SHIRTS, PANTS, HATS, AND SUNGLASSES.

OTHER INFORMATION

- PROTECT THE PRODUCT IN THIS CONTAINER FROM EXCESSIVE HEAT AND DIRECT SUN.

INACTIVE INGREDIENTS

Water, Butylene Glycol, Caprylic/Capric Triglyceride, Dimethicone, Cetearyl Alcohol, Cetearyl Olivate, Polyglyceryl-3 Diisostearate, Sorbitan Olivate, Chamomilla Recutita (Matricaria) Flower Extract, Aloe Barbadensis (Aloe Vera) Leaf Juice, Punica Granatum Fruit Extract, Cetearyl Glucoside, Triethoxycaprylylsilane, Tocopheryl Acetate, Xanthan Gum, Glycerin, Phenoxyethanol, Ethylhexylglycerin, Iron Oxides.